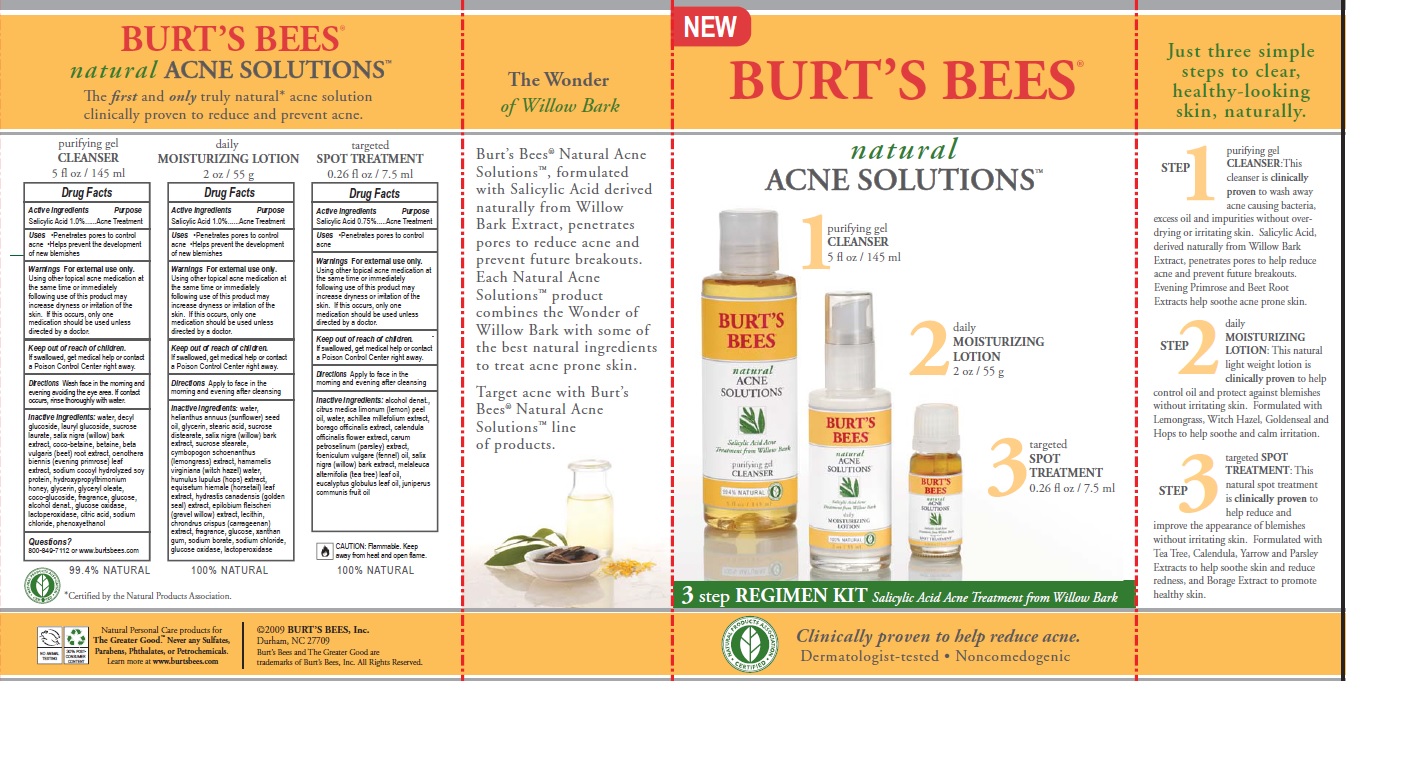 DRUG LABEL: Natural Acne Solutions 3 Step Regimen
NDC: 26052-035 | Form: KIT | Route: TOPICAL
Manufacturer: Burt's Bees
Category: otc | Type: HUMAN OTC DRUG LABEL
Date: 20160426

ACTIVE INGREDIENTS: SALICYLIC ACID 1 g/100 mL; SALICYLIC ACID 0.75 g/100 g; SALICYLIC ACID 1 g/100 g
INACTIVE INGREDIENTS: GLYCERYL OLEATE; DECYL GLUCOSIDE; LAURYL GLUCOSIDE; SUCROSE LAURATE; COCO GLUCOSIDE; GLUCOSE OXIDASE; GLYCERIN; HYDROXYPROPYLTRIMONIUM CHLORIDE FRAGMENT; BETA VULGARIS; HYDROLYZED SOY PROTEIN (ENZYMATIC; 2000 MW); ALCOHOL; LACTOPEROXIDASE BOVINE; ANHYDROUS CITRIC ACID; SODIUM CHLORIDE; PHENOXYETHANOL; WATER; SALIX NIGRA BARK; COCO-BETAINE; BETAINE; OENOTHERA BIENNIS LEAF; WATER; CALENDULA OFFICINALIS FLOWER; LEMON OIL; BORAGO OFFICINALIS SEED; PARSLEY OIL; SALIX NIGRA BARK; TEA TREE OIL; EUCALYPTUS GLOBULUS LEAF; FENNEL OIL; JUNIPER BERRY OIL; ALCOHOL; ACHILLEA MILLEFOLIUM; POTASSIUM SORBATE; HAMAMELIS VIRGINIANA LEAF; LEVOGLUCOSE; PHENOXYETHANOL; WATER; EPILOBIUM FLEISCHERI WHOLE; SUNFLOWER OIL; GLYCERIN; SALIX NIGRA BARK; WHITE WAX; CYMBOPOGON SCHOENANTHUS TOP; HUMULUS LUPULUS WHOLE; XANTHAN GUM; SUCROSE STEARATE; SODIUM CHLORIDE; GLUCOSE OXIDASE; EQUISETUM HYEMALE; LECITHIN, SOYBEAN; CHONDRUS CRISPUS CARRAGEENAN; SUCROSE; LACTOPEROXIDASE BOVINE; STEARIC ACID; HYDRASTIS CANADENSIS WHOLE

Active Ingredients

SALICYLIC ACID 1.0%

Purpose

Acne Treatment

INDICATIONS AND USAGE

PENETRATES PORES TO CONTROL ACNE.

HELPS PREVENT THE DEVELOPMENT OF NEW BLEMISHES

WARNINGS

FOR EXTERNAL USE ONLY. USING OTHER TOPICAL ACNE MEDICATION AT THE SAME TIME OR IMMEDIATELY FOLLOWING USE OF THIS PRODUCT MAY INCREASE DRYNESS OR IRRITATION OF THE SKIN. IF THIS OCCURS, ONLY ONE MEDICATION SHOULD BE USED UNLESS DIRECTED BY A DOCTOR.

Keep out of reach of children IF SWALLOWED, GET MEDICATL HELP OR CONTACT A POISON CONTROL CENTER RIGHT AWAY.

DIRECTIONS

APPLY TO FACE IN THE MORNING AND EVENING AFTER CLEANSING. IF BOTHERSOME DRYNESS OCCURS, REDUCE TO ONCE A DAY OR EVERY OTHER DAY.

INACTIVE INGREDIENTS

WATER, HELIANTHUS ANNUUS (SUNFLOWER) SEED OIL, GLYCERIN, STEARIC ACID, SUCROSE POLYSTEARATE, SALIX NIGRA (WILLOW) BARK EXTRACT, BEESWAX, CYMBOPOGON SCHOENANTHUS EXTRACT, HAMAMELIS VIRGINIANA (WITCH HAZEL) LEAF EXTRACT, HUMULUS LUPULUS (HOPS) EXTRACT, EQUISETUM HIEMALE EXTRACT, HYDRASTIS CANADENSIS (GOLDENSEAL) EXTRACT, EPILOBIUM FLEISCHERI EXTRACT, LECITHIN, CHONDRUS CRISPUS (CARAGEENAN), FRAGRANCE, GLUCOSE, XANTHAN GUM, SUCROSE, SUCROSE STEARATE, POTASSIUM SORBATE, SODIUM CHLORIDE, GLUCOSE OXIDASE, LACTOPEROXIDASE, PHENOXYETHANOL.

QUESTIONS?

800-849-7112 OR WWW.BURTSBEES.COM

ACTIVE INGREDIENTS

SALICYLIC ACID 1.0%

PURPOSE

ACNE TREATMENT

USES

PENETRATES PORES TO CONTROL ACNE.

HELPS PREVENT THE DEVELOPMENT OF NEW BLEMISHES.

WARNINGS

FOR EXTERNAL USE ONLY. USING OTHER TOPICAL ACNE MEDICATION AT THE SAME TIME OR IMMEDIATELY FOLLOWING USE OF THIS PRODUCT MAY INCREASE DRYNESS OR IRRITATION OF THE SKIN. IF THIS OCCURS, ONLY ONE MEDICATION WHOULD BE USED UNLESS DIRECTED BY A DOCTOR.

Keep out of reach of children. IF SWALLOWED, GET MEDICAL HELP OR CONTACT A POISON CONTROL CENTER RIGHT AWAY.

DIRECTIONS

WASH FACE IN THE MORNING AND EVENING AVOIDING THE EYE AREA. IF CONTACT OCCURS, RINSE THOROUGHLY WITH WATER.

QUESTIONS?

800-849-7112 OR WWW.BURTSBEES.COM

INACTIVE INGREDIENTS

WATER, DECYL GLUCOSIDE, LAURYL GLUCOSIDE, SUCROSE LAURATE, SALIX NIGRA (WILLOW) BARK EXTRACT, COCO-BETAINE, BETAINE, BETA VULGARIS (BEET) ROOT EXTRACT, CENOTHERA BIENNIS (EVENING PRIMROSE) LEAF EXTRACT, SODIUM COCOYL HYDROLYZED SOY PROTEIN, HYDROXYPROPYLTRIMONIUM HONEY, GLYCERIN, GLYCERYL OLEATE, COCO GLUCOSIDE, FRAGRANCE, GLUCOSE, ALCOHOL DENAT., GLUCOSE OXIDASE, LACTOPEROXIDASE, CITRIC ACID, SODIUM CHLORIDE, PHENOXYETHANOL.

ACTIVE INGREDIENT

Salicylic Acid 0.75%

PURPOSE

Acne Treatment

Uses

- Penetrates pores to control acne

Warnings

For external use only. Using other topical acne medication at the same time or immediately following use of this product may increased dryness or irritation of the skin. If this occurs, only one medication should be used unless directed by a doctor.

Keep out of reach of children. If swallowed, get medical help and contact a Poison Control Center right away.

Directions

Apply to face in the morning and evening after cleansing.

Inactive Ingredients

Inactive Ingredients: alcohol denat., citrus medica limonum (lemon) peel oil, water, achillea millefolium extract, borago officinalis extract, calendula officinalis flower extract, carum petroselinum (parsley) extract, foeniculum vulgare (fennel) oil, salix nigra (willow) bark extract, melaleuca alternifolia (tea tree) leaf oil, eucalyptus globulus leaf oil, juniperus communis fruit oil

Questions? 800-849-7112 or www.burtsbees.com

PACKAGE LABEL

BURTS BEES

Natural

ACNE SOLUTIONS

1 Purifying Gel Cleanser

2 Daily Moisturizing Lotion

3 Targeted Spot Treatment

3 Step Regimen Kit Salicylic Acid Acne Treatment from Willow Bark